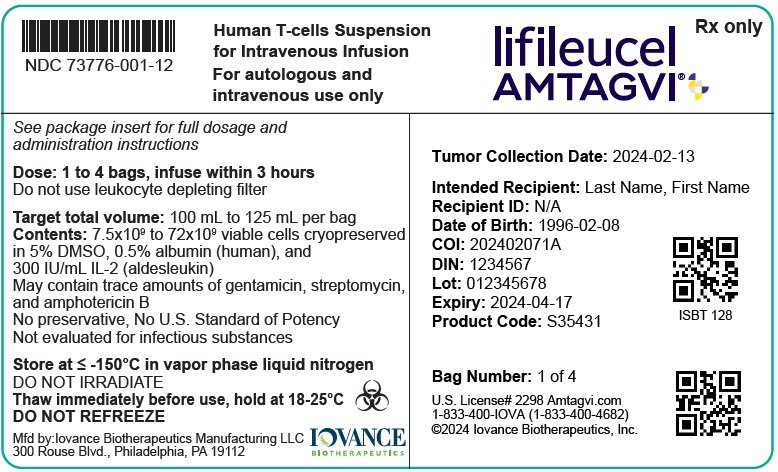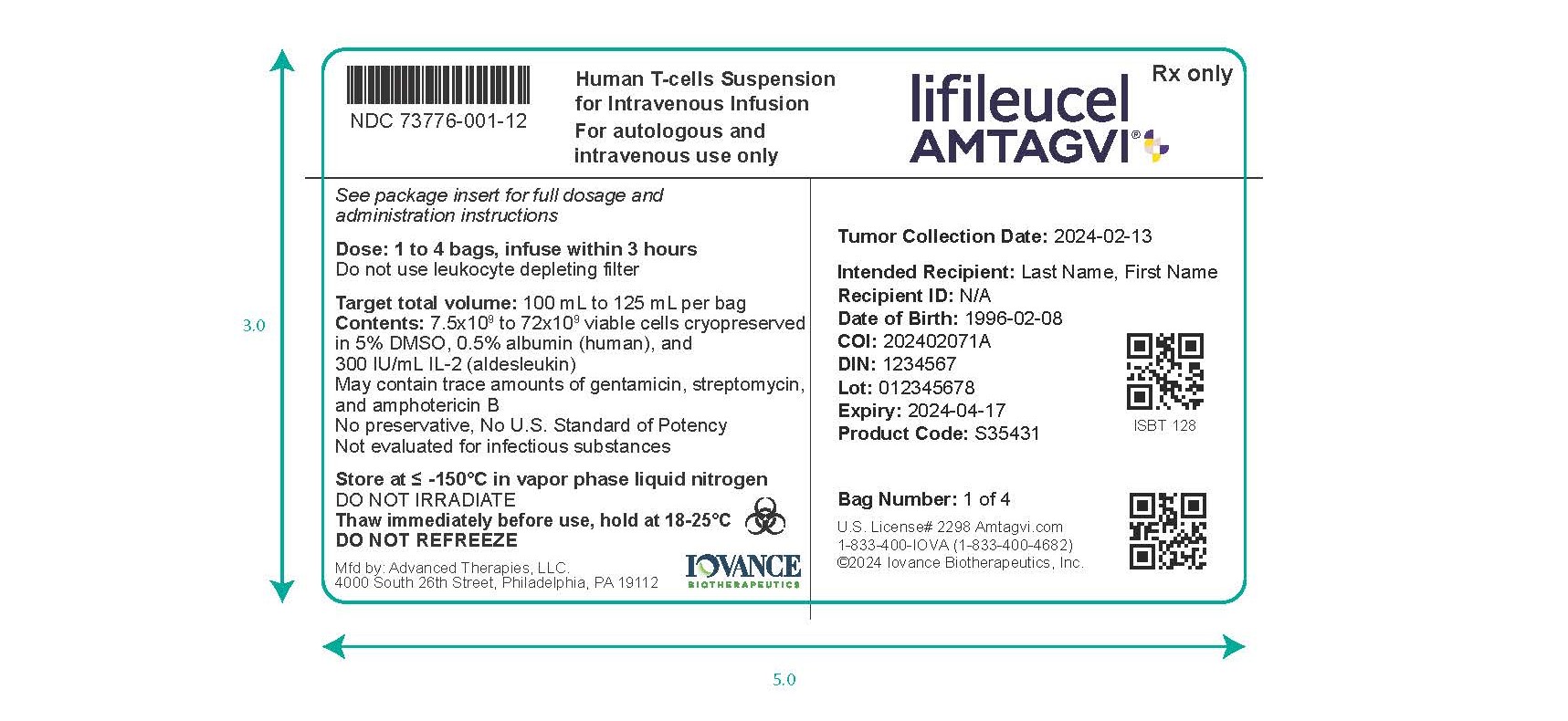 DRUG LABEL: AMTAGVI
NDC: 73776-001 | Form: SUSPENSION
Manufacturer: Iovance Biotherapeutics Inc.
Category: other | Type: CELLULAR THERAPY
Date: 20251014

ACTIVE INGREDIENTS: LIFILEUCEL 72000000000 1/500 mL
INACTIVE INGREDIENTS: DIMETHYL SULFOXIDE; ALDESLEUKIN; PLASMALYTE A

HIGHLIGHTS OF PRESCRIBING INFORMATION

These highlights do not include all the information needed to use AMTAGVI safely and effectively. See full prescribing information for AMTAGVI.
AMTAGVI (lifileucel) suspension for intravenous infusion
Initial U.S. Approval: 2024

WARNING: TREATMENT-RELATED MORTALITY, PROLONGED SEVERE CYTOPENIA, SEVERE INFECTION, CARDIOPULMONARY and RENAL IMPAIRMENT

See full prescribing information for complete boxed warning.

- Monitor patients for prolonged severe cytopenia and monitor for internal organ hemorrhage (5.1, 5.2, 5.3)
- Treat severe infections (5.1, 5.4)
- Monitor cardiopulmonary and renal functions throughout the treatment course (5.1, 5.5, 5.6, 5.7)

Administer in an inpatient hospital setting. An intensive care facility and specialists skilled in cardiopulmonary or intensive care medicine must be available (2.1, 6.1)

1 INDICATIONS AND USAGE

AMTAGVI is a tumor-derived autologous T cell immunotherapy indicated for the treatment of adult patients with unresectable or metastatic melanoma previously treated with a PD-1 blocking antibody, and if BRAF V600 mutation positive, a BRAF inhibitor with or without a MEK inhibitor. This indication is approved under accelerated approval based on objective response rate (ORR). Continued approval for this indication may be contingent upon verification and description of clinical benefit in a confirmatory trial(s) (1)

2 DOSAGE AND ADMINISTRATION

For autologous use only. For intravenous use only.

Verify the patient's identity prior to infusion.

- Administer AMTAGVI in an inpatient hospital setting with an intensive care facility (2.1)
- The AMTAGVI dose is between 7.5 × 10^9and 72 × 10^9viable cells (2.1)
- Administer a lymphodepleting regimen before infusion of AMTAGVI (2.2)
- Do NOT use a leukocyte depleting filter with AMTAGVI (2.2)
- Premedicate the patient with acetaminophen, or equivalent, and diphenhydramine, or another H1-antihistamine (2.2)
- Avoid prophylactic use of systemic corticosteroids (2.2)
- Administer entire dose of AMTAGVI (2.2)
- Administer IL-2 (aldesleukin) after infusion of AMTAGVI (2.2)
- See Full Prescribing Information for instructions on receipt, preparation, and administration of AMTAGVI (2.2, 16)

3 DOSAGE FORMS AND STRENGTHS

- AMTAGVI is a cell suspension for intravenous infusion (3)
- A single dose of AMTAGVI contains 7.5 × 10^9to 72 × 10^9viable cells suspended in 1 to 4 patient-specific infusion bag(s) (3)

4 CONTRAINDICATIONS

None (4)

5 WARNINGS AND PRECAUTIONS

Hypersensitivity reactions: Monitor for hypersensitivity reactions during infusion (5.8)

6 ADVERSE REACTIONS

The most common (incidence of greater than or equal to 20%) non-laboratory adverse reactions in order of decreasing frequency were chills, pyrexia, fatigue, tachycardia, diarrhea, febrile neutropenia, edema, rash, hypotension, alopecia, infection, hypoxia, and dyspnea (6.1)

To report SUSPECTED ADVERSE REACTIONS, contact Iovance Biotherapeutics, Inc. at 1-833-400-IOVA (4682) or FDA at 1-800-FDA-1088 or www.fda.gov/medwatch.

FULL PRESCRIBING INFORMATION

WARNING: TREATMENT-RELATED MORTALITY, PROLONGED SEVERE CYTOPENIA, SEVERE INFECTION, CARDIOPULMONARY and RENAL IMPAIRMENT

- Monitor patients for prolonged severe cytopenia and monitor for internal organ hemorrhage [see Warnings and Precautions (5.1,5.2,5.3)].
- Administer filgrastim or a biosimilar product to patients beginning Day 1 after AMTAGVI and continuing daily until the absolute neutrophil count (ANC) is greater than 1000 per mm^3for 3 consecutive days, or per institutional standard.
- Treat severe infections [see Warnings and Precautions (5.1, 5.4)].
- Monitor cardiopulmonary and renal functions throughout the treatment course. [see Warnings and Precautions (5.1, 5.5, 5.6, 5.7)].

Administer in an inpatient hospital setting. An intensive care facility and specialists skilled in cardiopulmonary or intensive care medicine must be available [see Dosage and Administration (2.1), and Adverse Reactions (6.1)] .

1 INDICATIONS AND USAGE

AMTAGVI is a tumor-derived autologous T cell immunotherapy indicated for the treatment of adult patients with unresectable or metastatic melanoma previously treated with a PD-1 blocking antibody, and if BRAF V600 mutation positive, a BRAF inhibitor with or without a MEK inhibitor.

This indication is approved under accelerated approval based on objective response rate (ORR) [see Clinical Studies (14)] . Continued approval for this indication may be contingent upon verification and description of clinical benefit in a confirmatory trial(s).

2 DOSAGE AND ADMINISTRATION

For autologous use only. For intravenous use only.

Verify the patient's identity prior to infusion.

2.1 Dose

Administer in an inpatient hospital setting under the supervision of a physician experienced in the use of anticancer agents. An intensive care facility and specialists skilled in cardiopulmonary or intensive care medicine must be available.

AMTAGVI is provided as a single dose for infusion containing a suspension of tumor-derived T cells. The dose is supplied in 1 to 4 patient-specific IV infusion bag(s) in individual protective metal cassettes. Each dose contains 7.5 × 10^9to 72 × 10^9viable cells.

2.2 Administration

AMTAGVI is for autologous use only.

The patient's identity must match the patient identifiers on the AMTAGVI cassette(s) and infusion bag(s).

Preparing Patient for AMTAGVI Infusion

Confirm availability of AMTAGVI and IL-2 (aldesleukin) prior to starting the lymphodepleting regimen.

Pretreatment

Administer a lymphodepleting chemotherapy regimen of cyclophosphamide 60 mg/kg intravenously with mesna daily for 2 days followed by fludarabine 25 mg/m^2intravenously daily for 5 days before infusion of AMTAGVI.

Infuse AMTAGVI as soon as possible after 24 hours have elapsed following the last dose of fludarabine, but no later than 4 days.

Premedication

Pre-medicate the patient with acetaminophen and diphenhydramine or another H1-antihistamine, approximately 30 to 60 minutes prior to AMTAGVI infusion.

Avoid prophylactic use of systemic corticosteroids which may interfere with the activity of AMTAGVI.

Receipt of AMTAGVI

AMTAGVI is shipped directly to the treatment center in the vapor phase of a liquid nitrogen cryoshipper. All treatment centers should have onsite storage in vapor phase of liquid nitrogen.

Product and patient-specific labels are located on both the product infusion bag(s) and protective metal cassette(s), which are inside the liquid nitrogen cryoshipper.

- Match the identity of the patient with the patient identifiers on the cassette(s) and infusion bag(s) upon receipt.
- Confirm the number of AMTAGVI cassette(s) and infusion bag(s) matches the total number of cassettes and infusion bags on the shipment packing slip.
- Store AMTAGVI frozen in the vapor phase of liquid nitrogen (less than or equal to minus 150°C).

Administration of AMTAGVI

The AMTAGVI dose is contained in 1 to 4 cryopreserved patient-specific infusion bag(s) in individual protective metal cassette(s). Thaw and infuse 1 bag at a time if more than 1 bag has been provided. Wait to thaw the next bag until the previous bag has been safely and completely administered.

Preparation of AMTAGVI

Do not thaw the product until it is ready to be infused. Coordinate the timing of AMTAGVI thaw and infusion. Confirm the infusion time in advance and adjust the start time for thaw so that AMTAGVI is available for infusion when the patient is ready. Once 1 bag of AMTAGVI is thawed, the infusion should be started as soon as possible and must be completed within 3 hours at room or ambient temperature (18°C to 25°C).

1. Confirm the availability of IL-2 (aldesleukin).
2. Prior to AMTAGVI preparation, match the recipient's identity with the patient identifiers on the AMTAGVI cassette label. Do not remove the AMTAGVI infusion bag from the cassette if the patient identifiers on the AMTAGVI cassette label do not match the intended patient. Contact Iovance Biotherapeutics, Inc. at 1-833-400-IOVA if there are any discrepancies.
3. Once recipient identification on the cassette is confirmed, remove the AMTAGVI infusion bag from the cassette. Check that the patient identifiers on the cassette label match the patient identifiers on the AMTAGVI infusion bag label and match the recipient's identity with the patient identifiers on the AMTAGVI infusion bag label. Contact Iovance Biotherapeutics, Inc. at 1-833-400-IOVA if there are any discrepancies.
4. Inspect each bag for any breaks or cracks prior to thawing. Inspect the spike ports for any damage prior to thawing. If a bag is damaged or compromised, do not infuse the contents and contact Iovance Biotherapeutics, Inc. at 1-833-400-IOVA.
5. For thawing, place the infusion bag inside a second sealable bag (preferably sterile) per local guidelines in case of a leak and to protect ports from contamination.
6. Thaw AMTAGVI at approximately 35°C to 39°C using either a water bath or a dry thaw method until there is no visible ice or frozen contents in the infusion bag. Total time from start of thaw until completion of thawing should be no more than 10 minutes.
7. Immediately remove bag from thawing device. Remove the infusion bag from the sealable plastic bag and wipe dry. Do not wash, spin down, or resuspend AMTAGVI in new media prior to infusion.
8. Once thawed, administer each bag of AMTAGVI as soon as possible. If needed, AMTAGVI may be maintained at room temperature (18°C to 25°C) not to exceed 3 hours. Do not re-freeze or refrigerate thawed product.
9. Prior to infusion, inspect the contents of the thawed infusion bag. If cell clumps are visible, gently mix the contents of the bag by inverting the bag prior to infusion. If needed, gently massage the bag to disperse cell clumps. Do not infuse the contents of an infusion bag if it is damaged or leaking, or otherwise appears to be compromised.

Infusion of AMTAGVI

1. Before infusion, the patient's health status should be reassessed and confirmed to be acceptable prior to AMTAGVI and IL-2 administration.
2. Confirm the patient's identity matches with the patient identifiers on the infusion bag.
3. Do NOT use a leukocyte depleting filter with AMTAGVI.
4. Prime the tubing with normal saline prior to infusion.
5. Initiate the infusion. Infuse the entire contents of each bag as soon as possible but within 3 hours of thawing.
6. Administer AMTAGVI at an infusion rate of approximately 1 mL per minute for the initial 5 minutes; thereafter 5 mL to 10 mL per minute.
7. Contents of all bags must be infused to complete a single dose. After the last bag is infused, rinse the tubing with normal saline at the same infusion rate to ensure all product is delivered.

AMTAGVI contains human cells. Follow universal and local biosafety guidelines applicable for the handling and disposal of AMTAGVI to avoid potential transmission of infectious diseases.

Administration of IL-2 (aldesleukin)

Beginning 3 to 24 hours after AMTAGVI infusion, administer intravenous IL-2 (aldesleukin) at 600,000 IU/kg every 8 to 12 hours for up to a maximum of 6 doses to support cell expansion in vivo. IL-2 (aldesleukin) should be administered in an inpatient setting under the supervision of a physician experienced in the use of anticancer agents.

3 DOSAGE FORMS AND STRENGTHS

AMTAGVI is a cell suspension for intravenous infusion.

A single dose of AMTAGVI contains 7.5 × 10^9to 72 × 10^9viable cells suspended in a cryopreservation medium. A single dose is split into 1 to 4 patient-specific infusion bag(s) (100 mL to 125 mL per bag) in individual protective metal cassettes [see How Supplied/Storage and Handling (16)] .

4 CONTRAINDICATIONS

None.

5 WARNINGS AND PRECAUTIONS

5.1 Treatment-Related Mortality

AMTAGVI is associated with treatment-related mortality. In the clinical trial, the treatment-related mortality rate was 7.5% (N=160), including 2 deaths during the lymphodepleting period, 6 deaths within 30 days, and 4 deaths 38 to 150 days following AMTAGVI administration. Adverse reactions associated with these deaths included severe infections (sepsis, pneumonia and encephalitis), internal organ hemorrhage (abdominal hemorrhage and intracranial hemorrhage), acute renal failure, acute respiratory failure, cardiac arrythmia, extensive ascites, liver injury, and bone marrow failure. Because clinical trials are conducted under widely varying conditions, treatment-related mortality rates observed in the clinical trials of a drug may not reflect the rates observed in practice.

5.2 Prolonged Severe Cytopenia

Patients treated with AMTAGVI may exhibit Grade 3 or higher cytopenia for weeks or longer. Based on adverse event reporting, Grade 3 or higher cytopenia or pancytopenia which did not resolve to less than or equal to Grade 2 or lasted beyond 30 days post AMTAGVI infusion occurred in 45.5% of melanoma patients who received AMTAGVI. Prolonged cytopenia included thrombocytopenia (30.1%), lymphopenia (19.9%), neutropenia (17.3%), leukopenia (14.7%), and pancytopenia (1.3%). Monitor blood counts after AMTAGVI infusion.

5.3 Internal Organ Hemorrhage

Patients treated with AMTAGVI may exhibit internal organ hemorrhage. Intraabdominal and intracranial hemorrhage can be life-threatening and have been associated with at least two deaths in patients who received AMTAGVI. Withhold or discontinue AMTAGVI infusion if internal organ hemorrhage is indicated, or patient is deemed ineligible for IL-2 (aldesleukin) infusion. Patients with persistent or repeated thrombocytopenia after receiving AMTAGVI should not use anticoagulants or must be under close monitoring if the patient must take anticoagulants.

5.4 Severe Infection

Severe, life-threatening, or fatal infections occurred in patients after AMTAGVI infusion. AMTAGVI treatment-related infections (any severity) occurred in 26.9% of patients with melanoma. Grade 3 or higher infections occurred in 13.5% of patients, including 10.9% of patients with infections of an unspecified pathogen and 3.8% of patients with infections of a specified pathogen.

Do not administer AMTAGVI to patients with clinically significant systemic infections. Monitor patients for signs and symptoms of infection before and after AMTAGVI infusion and treat appropriately. Administer prophylactic antimicrobials according to institutional guidelines.

Febrile neutropenia was observed in 46.8% of patients with melanoma after AMTAGVI Infusion. In the event of febrile neutropenia, evaluate for infection and manage with broad-spectrum antibiotics, fluids, and other supportive care as medically indicated.

5.5 Cardiac Disorder

Patients treated with AMTAGVI may exhibit cardiac disorder. Grade 3 or higher cardiac disorders related to the AMTAGVI regimen occurred in 9.0% (14/156) of patients who received AMTAGVI including tachycardia, atrial fibrillation, arrhythmia, acute myocardial infarction, cardiac ventricular thrombosis, cardiomyopathy, QT-prolongation. Cardiac arrhythmia resulted in one death among melanoma patients who received AMTAGVI.

Monitor patients with signs and symptoms of cardiac disorder before and after AMTAGVI infusion. Withhold or discontinue AMTAGVI infusion, if severe cardiac disorder is indicated, or patient is deemed ineligible for IL-2 (aldesleukin) infusion.

5.6 Respiratory Failure

Patients treated with AMTAGVI may develop worsened respiratory function which has been associated with deaths. Monitor patients with signs and symptoms of respiratory failure before and after AMTAGVI infusion. Withhold or discontinue AMTAGVI infusion if severe acute respiratory failure is indicated, or patient is deemed ineligible for IL-2 (aldesleukin) infusion.

5.7 Acute Renal Failure

Patients treated with AMTAGVI may develop worsened renal function which has been associated with deaths. Monitor patients with signs and symptoms of acute renal failure before and after AMTAGVI infusion. Withhold or discontinue AMTAGVI if severe acute renal injury is indicated, or patient is deemed ineligible for IL-2 (aldesleukin) infusion.

5.8 Hypersensitivity Reactions

Allergic reactions including serious hypersensitivity (e.g., anaphylaxis) may occur with the infusion of AMTAGVI.

Acute infusion reactions (defined as occurring within 1 day of infusion) may occur and include fever, rigors or chills, tachycardia, rash, hypotension, dyspnea, cough, chest tightness, and wheezing. These events generally resolve on the same day of infusion. Patients should be monitored during and after infusion for signs and symptoms of a severe reaction, and treated promptly.

6 ADVERSE REACTIONS

The most common (incidence of greater than or equal to 20%) non-laboratory adverse reactions in order of decreasing frequency were chills, pyrexia, fatigue, tachycardia, diarrhea, febrile neutropenia, edema, rash, hypotension, alopecia, infection, hypoxia, and dyspnea.

The serious adverse reactions included:

- Treatment-Related Mortality [see Warnings and Precautions (5.1)]
- Prolonged Severe Cytopenia [see Warnings and Precautions (5.2)]
- Internal Organ Hemorrhage [see Warnings and Precautions (5.3)]
- Severe Infection [see Warnings and Precautions (5.4)]
- Cardiac Disorder [see Warnings and Precautions (5.5)]
- Respiratory Failure [see Warnings and Precautions (5.6)]
- Acute Renal Failure [see Warnings and Precautions (5.7)]
- Hypersensitivity Reactions [see Warnings and Precautions (5.8)]

6.1 Clinical Trials Experience

Because clinical trials are conducted under widely varying conditions, adverse reaction rates observed in the clinical trials of a drug cannot be directly compared to rates in the clinical trials of another drug and may not reflect the rates observed in practice.

The pooled safety data described in this section reflect exposure to AMTAGVI within a regimen that included cyclophosphamide, fludarabine, and IL-2 (aldesleukin) in the global, multicenter, multicohort, open-label, single-arm clinical study in which 156 adult patients with unresectable or metastatic melanoma received a single infusion of AMTAGVI [see Clinical Studies (14)] . The median age of the study population was 56 years (range: 20 to 79 years); 53.8% were men. The performance status prior to tumor procurement was 68.6% with ECOG 0 and 31.4% with ECOG 1.

Table 1 summarizes the adverse reactions that occurred in at least 10% of patients treated with AMTAGVI and Table 2 describes the laboratory abnormalities of Grade 3 or 4 that occurred in at least 10% of patients.

Table 1: Adverse Reactions Observed in at Least 10% of Melanoma Patients Treated with AMTAGVI (N=156)
Adverse Reaction | Any Grade n (%) | Grade 3 or Higher n (%)
Blood and lymphatic system disorders
Febrile neutropenia | 73 (46.8) | 73 (46.8)
Cardiac disorders
Tachycardia [Tachycardia includes tachycardia and sinus tachycardia, atrial fibrillation, supraventricular tachycardia.] | 74 (47.4) | 12 (7.7)
Gastrointestinal disorders
Diarrhea | 73 (46.8) | 3 (1.9)
Vomiting | 68 (43.6) | 2 (1.3)
Nausea | 107 (68.6) | 4 (2.6)
General disorders and administration site conditions
Chills | 118 (75.6) | 8 (5.1)
Pyrexia | 95 (60.9) | 16 (10.3)
Fatigue [Fatigue includes fatigue, asthenia, and malaise.] | 87 (55.8) | 8 (5.1)
Edema [Edema includes edema, face edema, generalized edema, localized edema, edema peripheral, peripheral swelling, edema genital, scrotal edema, brain edema, catheter site edema, conjunctival edema, eyelid edema, laryngeal edema, macular edema, periorbital edema, pulmonary edema, vasogenic cerebral edema, and lymphoedema.] | 66 (42.3) | 8 (5.1)
Investigations
Weight increased | 30 (19.2) | 2 (1.3)
Infections and Infestations | 42 (26.9) | 21 (13.5)
Infection with pathogen unspecified [Infection with unspecified pathogen includes cellulitis, conjunctivitis, cystitis, dermatitis infected, device related infection, diarrhea infectious, endocarditis, enterocolitis infectious, infection, meningitis, nasopharyngitis, neutropenic sepsis, pneumonia, pyuria, rash pustular, respiratory tract infection (RTI), rhinitis, sepsis, sinusitis, skin infection, urinary tract infection (UTI).] | 30 (19.2) | 17 (10.9)
Infection with pathogen specified [Infection with mentioned pathogen includes bacteremia, candida infection, clostridium difficile colitis, cytomegalovirus infection or reactivation, Epstein-Barr virus infection, escherichia bacteremia, fungal skin infection, herpes simplex, herpes zoster, metapneumovirus infection, oral herpes, oral candidiasis, pneumonia klebsiella, respiratory syncytial virus infection, skin candida, tuberculosis.] | 19 (12.2) | 6 (3.8)
Metabolism and nutrition disorders
Decreased appetite | 48 (30.8) | 2 (1.3)
Nervous system disorders
Headache | 33 (21.2) | 1 (0.6)
Encephalopathy [Encephalopathy includes encephalopathy, automatism, cognitive disorder, confusional state, depressed level of consciousness, disturbance in attention, hypersomnia, lethargy, leukoencephalopathy, memory impairment, mental status changes, paranoia, somnolence, and stupor.] | 27 (17.3) | 9 (5.8)
Renal and urinary disorders
Acute kidney injury [Acute kidney injury includes acute kidney injury, anuria, azotemia, renal failure, renal tubular dysfunction, renal tubular necrosis, oliguria, and blood creatinine increased.] | 31 (19.9) | 11 (7.1)
Hematuria | 22 (14.1) | 2 (1.3)
Respiratory, thoracic and mediastinal disorders
Hypoxia [Hypoxia includes hypoxia and oxygen saturation decreased.] | 37 (23.7) | 19 (12.2)
Dyspnea [Dyspnea includes dyspnea, acute respiratory failure, orthopnea, respiratory distress, respiratory failure, and dyspnea exertional] | 34 (21.8) | 13 (8.3)
Skin and subcutaneous tissue disorders
Rash [Rash includes rash, rash generalized, rash maculo-papular, rash papular, rash pruritic, rash erythematous, and rash macular.] | 58 (37.2) | 15 (9.6)
Alopecia | 48 (30.8) | 0 (0)
Pruritus | 21 (13.5) | 0 (0)
Vascular disorders
Hypotension [Hypotension includes hypotension, blood pressure decreased, blood pressure systolic decreased, blood pressure diastolic decreased, and orthostatic hypotension.] | 58 (37.2) | 17 (10.9)
Capillary leak syndrome | 21 (13.5) | 7 (4.5)
Hypertension [Hypertension includes hypertension, blood pressure increased, blood pressure systolic increased, and blood pressure diastolic increased.] | 21 (13.5) | 11 (7.1)
Adverse Reactions occurred from AMTAGVI infusion to 6 months (182 days) post infusion.

Adverse reactions that occurred in less than 10% of patients treated with AMTAGVI included the following:

- Eye disorders:Uveitis (4.5%). Other eye disorders included Grade 1 or 2 retinal detachment, vision blurred, visual impairment, periorbital edema, visual acuity reduced, and retinal hemorrhage.
- Immune system disorders:Infusion related reaction (6.4%), anaphylactic reaction (1.3%), and cytokine release syndrome (3.2%).
- Skin and subcutaneous tissue disorders:Vitiligo (7.1%).

Table 2: Grade 3 or 4 Laboratory Abnormalities Occurring in at Least 10% of Melanoma Patients Following Treatment with AMTAGVI (N=156)
Laboratory Abnormality | Grades 3 or 4 (%)
Thrombocytopenia | 122 (78.2)
Neutropenia | 108 (69.2)
Anemia | 91 (58.3)
Leukopenia | 73 (46.8)
Lymphopenia | 66 (42.3)
Hypophosphatemia | 40 (25.6)
Frequency of Grade 3 or 4 laboratory abnormalities from AMTAGVI infusion to 6 months (182 days) post infusion.

Serious Adverse Reactions

Serious adverse reactions leading to death included acute respiratory failure (n=1), renal failure (n=2), cardiac arrhythmia (n=1), severe infections (n=4) including sepsis and septic shock, pneumonia, and encephalitis, internal organ hemorrhage (n=2), ascites and liver injury (n=1) and bone marrow failure (n=1).

Deaths

Among 160 patients with unresectable, or metastatic melanoma who initiated the AMTAGVI regimen, there were 12 deaths (7.5%), including 2 deaths during the lymphodepleting period, 6 deaths within 30 days following AMTAGVI administration, and additional 4 deaths 38 to 150 days following AMTAGVI administration. Adverse reactions associated with these deaths included severe infections (sepsis, pneumonia and encephalitis), internal organ hemorrhage (abdominal hemorrhage and intracranial hemorrhage), acute renal failure, acute respiratory failure, cardiac arrythmia, extensive ascites and liver injury and bone marrow failure.

8 USE IN SPECIFIC POPULATIONS

8.1 Pregnancy

Risk Summary

There are no available data with AMTAGVI use in pregnant women. No animal reproductive and developmental toxicity studies have been conducted with AMTAGVI. Therefore, AMTAGVI is not recommended for women who are pregnant, and pregnancy after AMTAGVI administration should be discussed with the treating physician. Report pregnancies to Iovance Biotherapeutics, Inc. at 1-833-400-IOVA.

In the U.S. general population, the estimated risk of major birth defects and miscarriage in clinically recognized pregnancies is 2% to 4% and 15% to 20%, respectively.

8.2 Lactation

Risk Summary

There is no information regarding the presence of AMTAGVI in human milk, the effect on the breastfed infant, and the effects on milk production. The developmental and health benefits of breastfeeding should be considered along with the mother's clinical need for AMTAGVI and any potential adverse effects on the breastfed infant from AMTAGVI or from the underlying maternal condition.

8.3 Females and Males of Reproductive Potential

Pregnancy Testing

The pregnancy status of women of child-bearing potential should be verified. Sexually active females of reproductive potential should have a pregnancy test prior to starting treatment with AMTAGVI.

Infertility

There are no data on the effect of AMTAGVI on fertility.

8.4 Pediatric Use

The safety and efficacy of AMTAGVI have not been established in pediatric patients.

8.5 Geriatric Use

Of 156 patients with unresectable or metastatic melanoma who were treated with AMTAGVI in clinical studies, 37 patients (23.7%) were 65 years of age or older. No differences in safety or effectiveness were observed between elderly patients and younger patients.

11 DESCRIPTION

AMTAGVI (lifileucel) is a tumor-derived autologous T cell immunotherapy comprised of a suspension of tumor-derived T cells for intravenous infusion. AMTAGVI is manufactured from resected patient tumor tissue prosected from one or more tumor lesions. Immune cells derived from a patient's tumor(s) are expanded in cell culture, washed, formulated as a cell suspension, and cryopreserved. The product must pass a sterility test before release for shipping as a frozen suspension in 1 to 4 patient-specific infusion bag(s) in individual protective metal cassettes. The product is thawed prior to administration back into the same patient [see Dosage and Administration (2.2), How Supplied/Storage and Handling (16)] .

AMTAGVI is composed primarily of T cells of the CD4+T and CD8+T cell lineages. AMTAGVI may also contain monocytes and other lymphocytes, including B cells and NK cells. AMTAGVI may contain viable melanoma tumor cells from the original tumor tissue used to manufacture the product.

The formulation contains 48% PlasmaLyte A, 50% CryoStor CS10 (resulting in final concentration of 5% dimethyl sulfoxide (DMSO)), 2% of 25% human serum albumin (resulting in a final concentration of 0.5% albumin), and 300 IU/mL IL-2 (aldesleukin).

A single dose of AMTAGVI is provided in 1 to 4 infusion bag(s) containing 100 mL to 125 mL of viable cells per bag in individual protective cassettes.

12 CLINICAL PHARMACOLOGY

12.1 Mechanism of Action

The specific mechanism of action of AMTAGVI (lifileucel) is unknown.

12.2 Pharmacodynamics

Pharmacodynamic activity was evaluated by measuring longitudinal changes of cytokines and chemokines (IL-15, IL-6, IL-7, IL-9, IL-10, IL-12(p40), CCL2, CXCL10, IFN-γ, and TNF-α) using plasma samples collected at baseline and post-infusion of AMTAGVI up to Month 3. The mean level of IL-15 and CXCL10 peaked following lymphodepletion and administration of AMTAGVI at Day 1-4, decreased over time, and returned to baseline levels within 1-3 months. The mean IFN-γ level was below baseline post lymphodepletion and AMTAGVI infusion at Day 1-4 and returned to baseline by Day 14. Other cytokines and chemokines listed above did not show any noticeable changes. No difference was observed in the cytokines and chemokines level between responding and non-responding patients.

12.3 Pharmacokinetics

The proportion of unique TCR clonotypes from the AMTAGVI lots contributing to the peripheral blood TCR repertoire among infused patients was analyzed using a semi-quantitative polymerase chain reaction followed by next generation sequencing. The proportion of TCR clones that are composed of clonotypes identified in the product increases from a mean of 16% (n=125) at pre-infusion to 83% at Day 4 after AMTAGVI infusion. The TCR clones declined to 51% at Day 14 (n=51) and remain 37% to 41% from Day 42 (n=120) to month 12 (n=37) post-infusion of AMTAGVI. No significant correlation was found between AMTAGVI persistence and efficacy.

13 NONCLINICAL TOXICOLOGY

13.1 Carcinogenesis, Mutagenesis, Impairment of Fertility

No carcinogenicity or genotoxicity studies have been conducted with AMTAGVI. No studies have been conducted to evaluate the effects of AMTAGVI on fertility.

14 CLINICAL STUDIES

The efficacy of a single treatment with AMTAGVI was evaluated in a global, multicenter, multicohort, open-label, single-arm clinical study. This study enrolled patients with unresectable or metastatic melanoma who had previously been treated with at least one systemic therapy, including a PD-1 blocking antibody, and if BRAF V600 mutation-positive, a BRAF inhibitor or BRAF inhibitor with MEK inhibitor. This study excluded patients with uncontrolled brain metastases, organ allograft or prior cell transfer, melanoma of uveal or ocular origin, systemic steroid therapy for any reason, Grade 2 or higher hemorrhage within 14 days prior to study enrollment (tumor resection), left ventricular ejection fraction (LVEF) less than 45% or New York Heart Association (NYHA) functional classification greater than Class 1, and patients with forced expiratory volume in one second (FEV1) of less than or equal to 60%.

There were 111 patients who underwent tumor resection of whom 22 (19.8%) patients did not receive AMTAGVI due to the following reasons: inability to manufacture AMTAGVI (n=6), disease related death (n=3), meeting exclusion criteria (n=5), disease progression (n=3), starting new anti-cancer therapy or consent withdrawal (n=3), or adverse events from lymphodepletion including one death (n=2). Among 89 patients who received AMTAGVI, two (2) patients were excluded because the product did not meet specification and five (5) patients were excluded due to product comparability.

The primary efficacy analysis set included 82 patients who received AMTAGVI. Among these, nine (9) patients received AMTAGVI at a dose less than 7.5 × 10^9viable cells and did not achieve an objective response. The recommended AMTAGVI dosing range was set at 7.5 × 10^9to 72 × 10^9viable cells (73 patients received this dosing range).

Median time from tumor tissue procurement to the end of the manufacturing process was 23 days and to infusion was 34 days. Lesion origin of AMTAGVI products included skin, lymph nodes, liver, lung, peritoneal, musculoskeletal, breast, and other anatomic sites including chest wall, abdominal wall, adrenal gland, abdominal-peritoneal, paraesophageal, axillary, thigh, back, supraclavicular, and soft tissue.

All 73 (100%) patients received prior anti-PD-(L)1 therapy, 63 (86.3%) received prior anti-CTLA-4 therapy, 42 (57.5%) received anti-PD1/anti-CTLA-4 combination therapy and 20 (27.4%) received a BRAF inhibitor or combination therapy with BRAF and MEK inhibitors. The median age was 58 years (min, max: 25, 74 years), with 26.0% age 65 or older, 52.1% were male, 94.5% were white, 2.7% were black, and 1.4% were Asian. Patients received a median of 3 prior lines of therapy and a median of 2 prior lines of anti-PD(L)1 containing therapies. Disease characteristics were: BRAF V600 mutation-positive: 27.4%; PD-L1 TPS greater than or equal 5%: 23.3%; elevated LDH: 63.0%; brain and/or liver metastases: 54.8%. The median target lesion sum of diameters was 108.7 mm (min, max: 15.7, 552.9). The performance status prior to tumor procurement was ECOG 0 (71.2%) and ECOG 1 (28.8%).

AMTAGVI was administered following a lymphodepleting regimen consisting of cyclophosphamide 60 mg/kg daily with mesna for 2 days followed by fludarabine 25 mg/m^2daily for 5 days. Three (3) to 24 hours after infusion, patients received IL-2 (aldesleukin) at 600,000 IU/kg every 8 to 12 hours for up to 6 doses in order to support cell expansion in vivo. The median administered AMTAGVI dose was 21.1× 10^9viable cells. The median number of administered IL-2 (aldesleukin) doses was 6.

Efficacy was established on the basis of objective response rate (ORR) and duration of response (DoR) (see Table 3). The median time to initial response to AMTAGVI was 1.5 months (min, max: 1.3, 4.2).

Table 3: Efficacy Results Among Patients Who Received AMTAGVI Dose Range of 7.5 × 10^9to 72 × 10^9Viable Cells
Endpoint [Per RECIST v1.1 assessed by Independent Review Committee (IRC).] | Efficacy Set (N=73)
Objective Response Rate
ORR, % (95% CI) | 31.5 (21.1, 43.4)
Complete response rate, n (%) | 3 (4.1)
Partial response rate, n (%) | 20 (27.4)
Duration of Response [Number of responders was N=23.] , [Kaplan-Meier estimate of median potential follow-up for DoR was 18.6 months.]
Median DoR in months (95% CI) [Kaplan-Meier estimate in months among all responders. DoR measured from the date of confirmed initial objective response to the date of progression or death from any cause.] | NR (4.1, NR)
Range [+ sign indicates a censored value] | (1.4+, 26.3+)
Patients with DoR ≥ 6 months [Observed proportion of patients with duration of response beyond landmark time] , n (%) | 13 (56.5)
Patients with DoR ≥ 9 months , n (%) | 11 (47.8)
Patients with DoR ≥ 12 months , n (%) | 10 (43.5)
CI, confidence interval; DoR, duration of response; NR, not reached; ORR, objective response rate.

Supporting pooled efficacy analysis included 189 patients who underwent tumor resection of whom 33 did not receive AMTAGVI due to the following reasons: inability to manufacture AMTAGVI (n=8), disease related death within 40 days after tumor harvest (n=5), meeting exclusion criteria (n=6), disease progression (n=6), starting new anti-cancer therapy or consent withdrawal (n=4), or adverse events from lymphodepletion including two deaths (n=4). Among the 156 patients who received AMTAGVI, 2 patients who received AMTAGVI that did not meet the product specification and 1 patient who received AMTAGVI below the protocol specified dosing range due to anaphylactic reaction were excluded.

The supporting pooled efficacy set included 153 patients. The median administered AMTAGVI dose was 21.1× 10^9viable cells and the median number of administered IL-2 (aldesleukin) doses was 6. The ORR was 31.4% (95% CI: 24.1%, 39.4%) with a CR of 5.2% (n=8) and PR of 26.1% (n=40). The median time to initial response to AMTAGVI was 1.5 months (min, max: 1.3, 4.2). The median DoR was not reached (range: 1.4+, 45.0+). Among responders, 62.5%, 56.3% and 54.2% maintained durable responses at 6, 9 and 12 months, respectively, following the initial response.

16 HOW SUPPLIED/STORAGE AND HANDLING

AMTAGVI is supplied in 1 to 4 infusion bag(s) (NDC 73776-001-11), with each bag containing approximately 100 mL to 125 mL of frozen suspension of tumor-derived T cells in 5% DMSO, 0.5% albumin (human), and 300 IU/mL IL-2 (aldesleukin). Each bag is contained within a protective metal cassette (NDC 73776-001-12). AMTAGVI is stored in the vapor phase of liquid nitrogen and supplied in a liquid nitrogen cryoshipper.

STORAGE AND HANDLING

Product and patient-specific labels are located on both the product infusion bag(s) and the protective shipping cassette(s), which are inside the liquid nitrogen cryoshipper.

- Match the identity of the patient with the patient identifiers on the cassette(s) and infusion bag(s) upon receipt.
- Confirm the number of AMTAGVI cassette(s) and infusion bag(s) matches the total number of cassette(s) and infusion bag(s) on the shipment packing slip.
- Store AMTAGVI frozen in the vapor phase of liquid nitrogen (less than or equal to minus 150°C).
- Thaw AMTAGVI immediately prior to infusion [see Dosage and Administration (2.2)] .

17 PATIENT COUNSELING INFORMATION

Advise the patient to read the FDA-approved patient labeling (Patient Information).

Prior to infusion, advise patients of the following risks:

Hypersensitivity Reactions:

Signs and symptoms associated with hypersensitivity reactions including fever, rigors or chills, tachycardia, rash, hypotension, dyspnea, cough, chest tightness, and wheezing [see Warnings and Precautions (5.8)] .

Prolonged Severe Cytopenia:

Signs or symptoms associated with bone marrow suppression (i.e., neutropenia, thrombocytopenia and anemia) for more than several weeks following lymphodepleting chemotherapy and AMTAGVI [ see Warnings and Precautions (5.2), Adverse Reactions (6.1)].

Severe Infection:

Signs and symptoms associated with severe infections. Advise patients that AMTAGVI treatment regimen will not be initiated if they have an ongoing uncontrolled infection. Anti-microbial prophylaxis and treatment of infection will be administered [ see Warnings and Precautions (5.4), Adverse Reactions (6.1)].

Internal Organ Hemorrhage:

Signs or symptoms of internal organ hemorrhage following AMTAGVI treatment regimen. Advise patients to seek immediate medical attention should signs or symptoms of internal organ hemorrhage occur at any time [ see Warnings and Precautions (5.3)].

Cardiopulmonary and Renal Impairment:

Signs or symptoms of cardiopulmonary or renal injuries following AMTAGVI treatment regimen. Advise patients to seek immediate medical attention should signs or symptoms of cardiopulmonary, or renal injury occur at any time [ see Warnings and Precautions (5.5, 5.6, 5.7)].

Manufactured by:
Advanced Therapeutics, LLC.
4000 South 26thStreet
Philadelphia, PA 19112

OR

Iovance Biotherapeutics Manufacturing LLC
300 Rouse Boulevard
Philadelphia, PA 19112

For specific manufacturing site used to manufacture the received AMTAGVI batch, see bag and cassette labels.

Marketed by:
Iovance Biotherapeutics Manufacturing LLC
300 Rouse Boulevard
Philadelphia, PA 19112
U.S. license number: 2298

© 2024 Iovance Biotherapeutics, Inc.

Patient Information AMTAGVI (pronounced am-tag-vee) (lifileucel)

What is the most important information I should know about AMTAGVI?

- You will likely be in a hospital prior to and after receiving AMTAGVI.

What is AMTAGVI?

AMTAGVI is a type of medicine called a 'Tumor-derived autologous T cell immunotherapy.' The active substance in the medicine is lifileucel, which is comprised of T cells derived from tissue excised from your tumor. Tumor-derived T cells are cells produced by the body's immune system that may recognize and kill cancer (tumor) cells.

AMTAGVI is used to treat adult patients with a type of skin cancer that cannot be removed surgically or has spread to other parts of the body called unresectable or metastatic melanoma. AMTAGVI is used when your melanoma has not responded or stopped responding to a PD-1 blocking drug either by itself or in a combination, and if your cancer is BRAF mutation positive, a BRAF inhibitor drug with or without a MEK inhibitor drug that also has stopped working.

Before taking AMTAGVI, tell your healthcare provider about all of your medical conditions, including if you:

- Have any lung, heart, liver or kidney problems
- Have low blood pressure
- Have a recent or active infection or other inflammatory conditions including cytomegalovirus (CMV) infection, hepatitis B or C or human immunodeficiency virus (HIV) infection
- Are pregnant, think you may be pregnant, or plan to become pregnant
- Are breastfeeding
- Notice the symptoms of your cancer are getting worse
- Have had a vaccination in the past 28 days or plan to have one in the next few months
- Have been taking blood thinner

Tell your healthcare provider about all the medications you take,including prescription and over-the-counter medicines, vitamins, and herbal supplements.

How will I receive AMTAGVI?

- AMTAGVI is made from your surgically removed tumor. Tumor derived T cells are grown in a manufacturing center at the end of which they number in the billions of cells.
- Your tumor tissue is sent to a manufacturing center to make AMTAGVI. It takes about 34 days from the time your tumor tissue is received at the manufacturing center until AMTAGVI is available to be shipped back to your healthcare provider, but the time may vary. Your AMTAGVI will be provided in 1 to 4 patient-specific infusion bag(s) containing 100 mL to 125 mL of viable (alive) cells per bag.
- After your AMTAGVI arrives at your treating institution, your healthcare provider will give you lymphodepleting chemotherapy to prepare your body.
- Approximately 30 to 60 minutes before you are given AMTAGVI, you may be given other medicines. These may include:
  - Medicines for an allergic reaction (anti-histamines)
  - Medicines for fever (such as acetaminophen)
- Your AMTAGVI will be provided in 1 to 4 infusion bag(s) containing 100 mL to 125 mL of viable cells per bag. When your body is ready for AMTAGVI infusion, your healthcare provider will give AMTAGVI to you by intravenous infusion. This usually takes less than one and a half hours.

After getting AMTAGVI

Beginning 3 to 24 hours after AMTAGVI is given, you may be given up to 6 doses of IL-2 (aldesleukin) every 8 to 12 hours via intravenous infusion. Your doctor may discontinue IL-2 (aldesleukin) infusion any time if you present severe side effects.

You will have to stay in the hospital until you have completed the IL-2 (aldesleukin) treatment and you have recovered from any serious side effects associated with the AMTAGVI treatment.

You should plan to stay within 2 hours of the location where you received your treatment for several weeks after getting AMTAGVI. Your healthcare provider will check to see if your treatment is working and help you with any side effects that occur.

What are the possible side effects of AMTAGVI?

The most common side effects of the AMTAGVI treatment include:

- Chills
- Fever (100.4°F (38°C) or higher)
- Low white blood cell count (may increase risk of infections)
- Fatigue
- Low red blood cell count (may cause you to feel tired or weak)
- Fast or irregular heartbeat
- Rash
- Low blood pressure
- Diarrhea

These are not all the possible side effects of the AMTAGVI treatment. If you would like more information about AMTAGVI, talk with your healthcare provider. You can ask your healthcare provider for information about AMTAGVI that is written for health professionals. You may report side effects to FDA at 1-800-FDA-1088.

Marketed by:
Iovance Biotherapeutics Manufacturing LLC
Philadelphia, PA 19112

PRINCIPAL DISPLAY PANEL - 125 mL Bag Cartridge Label - Iovance

NDC 73776-001-12

Human T-cells Suspension
for Intravenous Infusion
For autologous and
intravenous use only

lifileucel
AMTAGVI®

Rx only

See package insert for full dosage and
administration instructions

Dose: 1 to 4 bags, infuse within 3 hours

Do not use leukocyte depleting filter

Target total volume: 100 mL to 125 mL per bag

Contents: 7.5x10^9to 72x10^9viable cells cryopreserved
in 5% DMSO, 0.5% albumin (human), and
300 IU/mL IL-2 (aldesleukin)

May contain trace amounts of gentamicin, streptomycin,
and amphotericin B

No preservative, No U.S. Standard of Potency
Not evaluated for infectious substances

Store at ≤ -150°C in vapor phase liquid nitrogen

DO NOT IRRADIATE

Thaw immediately before use, hold at 18-25°C

DO NOT REFREEZE

Mfd by:Iovance Biotherapeutics Manufacturing LLC
300 Rouse Blvd., Philadelphia, PA 19112

IOVANCE
BIOTHERAPEUTICS

Tumor Collection Date: 2024-02-13

Intended Recipient: Last Name, First Name
Recipient ID: N/A
Date of Birth: 1996-02-08
COI: 202402071A
DIN: 1234567
Lot: 012345678
Expiry: 2024-04-17
Product Code: S35431

ISBT 128

Bag Number: 1 of 4

U.S. License# 2298 Amtagvi.com
1-833-400-IOVA (1-833-400-4682)
©2024 Iovance Biotherapeutics, Inc.

PRINCIPAL DISPLAY PANEL - 125 mL Bag Cartridge Label - WuXi

NDC 73776-001-12

Human T-cells Suspension
for Intravenous Infusion
For autologous and
intravenous use only

lifileucel
AMTAGVI®

Rx only

See package insert for full dosage and
administration instructions

Dose: 1 to 4 bags, infuse within 3 hours

Do not use leukocyte depleting filter

Target total volume: 100 mL to 125 mL per bag

Contents: 7.5x10^9to 72x10^9viable cells cryopreserved
in 5% DMSO, 0.5% albumin (human), and
300 IU/mL IL-2 (aldesleukin)

May contain trace amounts of gentamicin, streptomycin,
and amphotericin B

No preservative, No U.S. Standard of Potency
Not evaluated for infectious substances

Store at ≤ -150°C in vapor phase liquid nitrogen

DO NOT IRRADIATE

Thaw immediately before use, hold at 18-25°C

DO NOT REFREEZE

Mfd by: Advanced Therapies, LLC.
4000 South 26th Street, Philadelphia, PA 19112

IOVANCE
BIOTHERAPEUTICS

Tumor Collection Date: 2024-02-13

Intended Recipient: Last Name, First Name
Recipient ID: N/A
Date of Birth: 1996-02-08
COI: 202402071A
DIN: 1234567
Lot: 012345678
Expiry: 2024-04-17
Product Code: S35431

ISBT 128

Bag Number: 1 of 4

U.S. License# 2298 Amtagvi.com
1-833-400-IOVA (1-833-400-4682)
©2024 Iovance Biotherapeutics, Inc.